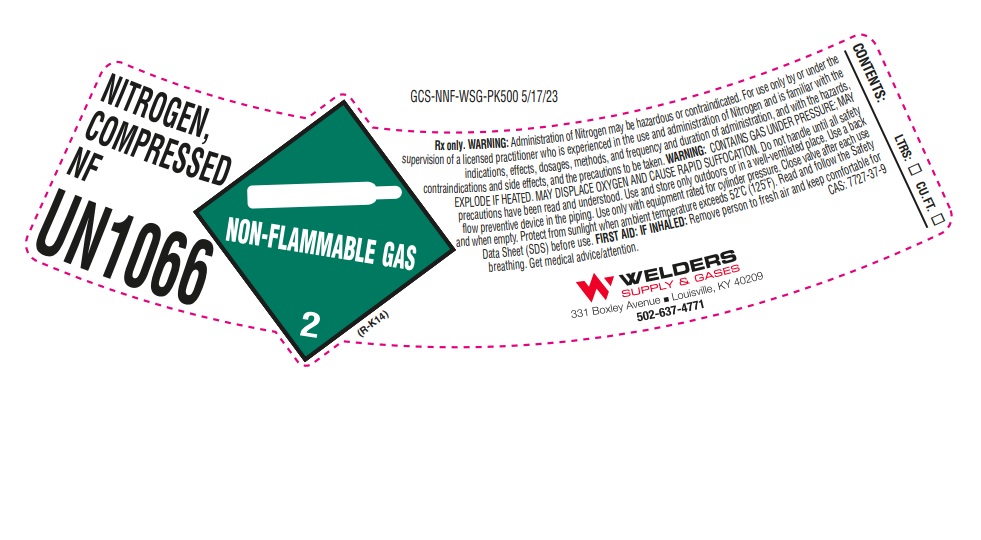 DRUG LABEL: Nitrogen
NDC: 84078-001 | Form: GAS
Manufacturer: WELDERS SUPPLY COMPANY OF LOUISVILLE, INC.
Category: prescription | Type: HUMAN PRESCRIPTION DRUG LABEL
Date: 20260128

ACTIVE INGREDIENTS: NITROGEN 992 mL/1 L

Nitrogen

PACKAGE LABEL

NITROGEN, COMPRESSED NF

UN1066

Rx only. WARNING: Administration of Nitrogen may be hazardous or contraindicated. For use only by or under the supervision of a licensed practitioner who is experienced in the use and administration of Nitrogen and is familiar with the indications, effects, dosages, methods, and frequency and duration of administration, and with the hazards, contraindications and side effects, and the precautions to be taken. WARNING: CONTAINS GAS UNDER PRESSURE; MAY EXPLODE IF HEATED. MAY DISPLACE OXYGEN AND CAUSE RAPID SUFFOCATION. Do not handle until all safety precautions have been read and understood. Use and store only outdoors or in a well-ventilated place. Use a back flow preventive device in the piping. Use only with equipment rated for cylinder pressure. Close valve after each use and when empty. Protect from sunlight when ambient temperature exceeds 52 C (125 F). Read and follow the Safety Data Sheet (SDS) before use. FIRST AID: IF INHALED: Remove person to fresh air and keep comfortable for breathing. Get medical advice/attention. CAS: 7727-37-9

CONTENTS: LTRS: CU.FT.

WELDERS SUPPLY & GASES

331 Boxley Avenue. Louisville, KY 40209

502-637-4771